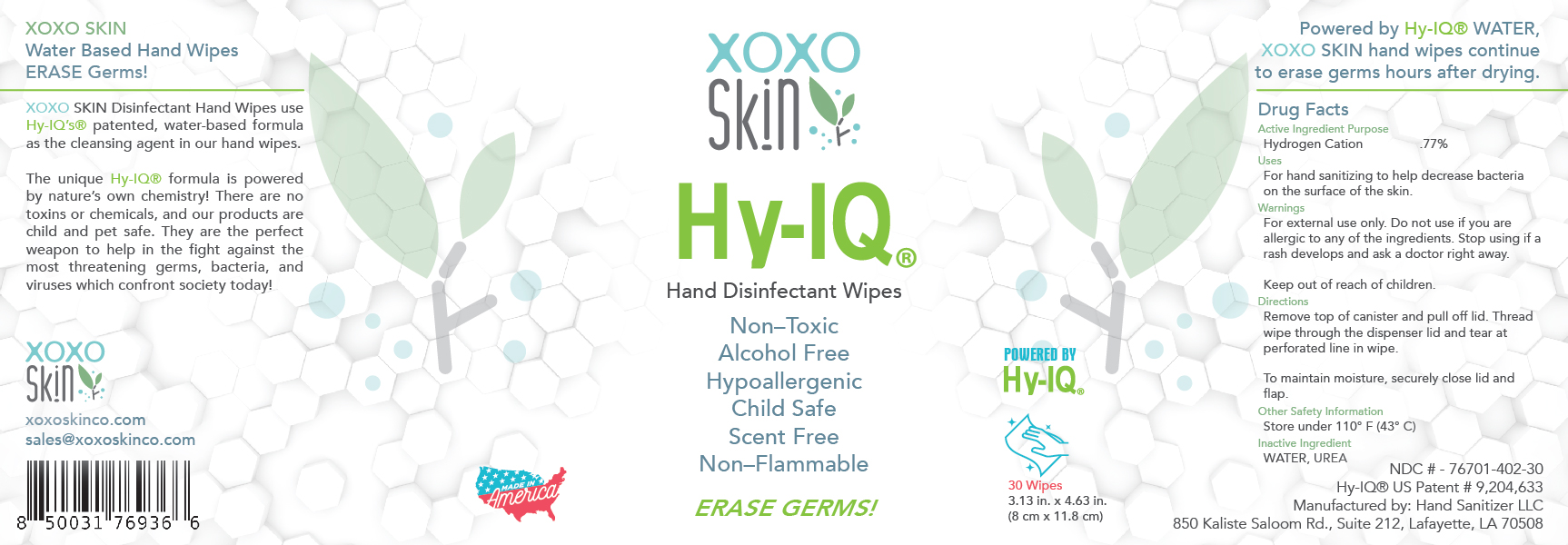 DRUG LABEL: XOXO HAND DISINFECTANT WIPES
NDC: 76701-402 | Form: CLOTH
Manufacturer: Hand Sanitizer LLC
Category: otc | Type: HUMAN OTC DRUG LABEL
Date: 20210911

ACTIVE INGREDIENTS: HYDROGEN CATION 10 mg/1 mL
INACTIVE INGREDIENTS: WATER 940 mg/1 mL; UREA 50 mg/1 mL

XOXO HAND DISINFECTANT WIPES

Active Ingredient

Hydrogen Cation .77%

Purpose

Antiseptic

Uses

For hand sanitizing to decrease bacteria on the surface of the skin.

Warnings

For external use only. Do not use if you are allergic to any of the ingredients. Stop using if a rash develops and ask a doctor right away.

Keep Out of Reach of Children

Directions

Remove top of canister and pull off lid. Thread wipe through the dispenser lid and tear at perforated line in wipe. To maintain moisture, securely close lid and flap.

Other Safety Information

Store under 110º F (43º C)

Inactive Ingredient

Water, Urea

XOXO HAND DISINFECTANT WIPES